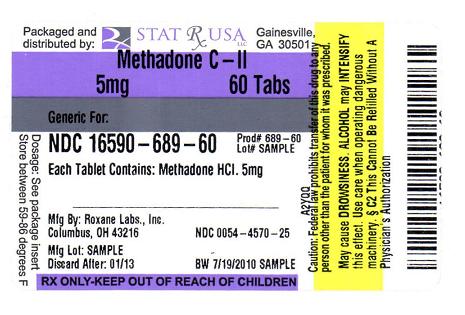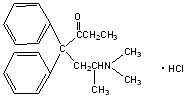 DRUG LABEL: METHADONE HYDROCHLORIDE
NDC: 16590-689 | Form: TABLET
Manufacturer: STAT Rx USA LLC
Category: prescription | Type: HUMAN PRESCRIPTION DRUG LABEL
Date: 20111105
DEA Schedule: CII

ACTIVE INGREDIENTS: METHADONE HYDROCHLORIDE 5 mg/1 1
INACTIVE INGREDIENTS: MAGNESIUM STEARATE; CELLULOSE, MICROCRYSTALLINE; STARCH, CORN

Rx Only

BOXED WARNING

Deaths, cardiac and respiratory, have been reported during initiation and conversion of pain patients to methadone treatment from treatment with other opioid agonists. It is critical to understand the pharmacokinetics of methadone when converting patients from other opioids (see DOSAGE AND ADMINISTRATION). Particular vigilance is necessary during treatment initiation, during conversion from one opioid to another, and during dose titration.

Respiratory depression is the chief hazard associated with methadone hydrochloride administration. Methadone's peak respiratory depressant effects typically occur later, and persist longer than its peak analgesic effects, particularly in the early dosing period. These characteristics can contribute to cases of iatrogenic overdose, particularly during treatment initiation and dose titration.

In addition, cases of QT interval prolongation and serious arrhythmia (torsades de pointes) have been observed during treatment with methadone. Most cases involve patients being treated for pain with large, multiple daily doses of methadone, although cases have been reported in patients receiving doses commonly used for maintenance treatment of opioid addiction.

Methadone treatment for analgesic therapy in patients with acute or chronic pain should only be initiated if the potential analgesic or palliative care benefit of treatment with methadone is considered and outweighs the risks.

Conditions For Distribution And Use Of Methadone Products For The Treatment Of Opioid Addiction

Code of Federal Regulations, Title 42, Sec 8

Methadone products when used for the treatment of opioid addiction in detoxification or maintenance programs, shall be dispensed only by opioid treatment programs (and agencies, practitioners or institutions by formal agreement with the program sponsor) certified by the Substance Abuse and Mental Health Services Administration and approved by the designated state authority. Certified treatment programs shall dispense and use methadone in oral form only and according to the treatment requirements stipulated in the Federal Opioid Treatment Standards (42 CFR 8.12). See below for important regulatory exceptions to the general requirement for certification to provide opioid agonist treatment.

Failure to abide by the requirements in these regulations may result in criminal prosecution, seizure of the drug supply, revocation of the program approval, and injunction precluding operation of the program.

Regulatory Exceptions To The General Requirement For Certification To Provide Opioid Agonist Treatment:

1. During inpatient care, when the patient was admitted for any condition other than concurrent opioid addiction (pursuant to 21CFR 1306.07(c)), to facilitate the treatment of the primary admitting diagnosis).
2. During an emergency period of no longer than 3 days while definitive care for the addiction is being sought in an appropriately licensed facility (pursuant to 21CFR 1306.07(b)).

DESCRIPTION

Methadone Hydrochloride Tablets, USP, for oral administration, each contain 5 mg or 10 mg of methadone hydrochloride.

Methadone hydrochloride is a white, crystalline material that is water-soluble.

Methadone hydrochloride is chemically described as 6-(dimethylamino)-4,4-diphenyl-3-hepatanone hydrochloride. Its molecular formula is C21H27NO · HCl and it has a molecular weight of 345.91. Methadone hydrochloride has a melting point of 235°C, and a pKa of 8.25 in water at 20°C. Its octanol/water partition coefficient at pH 7.4 is 117. A solution (1:100) in water has a pH between 4.5 and 6.5.

It has the following structural formula:

Other ingredients of Methadone Hydrochloride Tablets include: magnesium stearate, microcrystalline cellulose, and starch.

CLINICAL PHARMACOLOGY

Mechanism of Action

Methadone hydrochloride is a mu-agonist; a synthetic opioid analgesic with multiple actions qualitatively similar to those of morphine, the most prominent of which involves the central nervous system and organs composed of smooth muscle. The principal therapeutic uses for methadone are for analgesia and for detoxification or maintenance in opioid addiction. The methadone abstinence syndrome, although qualitatively similar to that of morphine, differs in that the onset is slower, the course is more prolonged, and the symptoms are less severe.

Some data also indicate that methadone acts as an antagonist at the N-methyl-D-aspartate (NMDA) receptor. The contribution of NMDA receptor antagonism to methadone’s efficacy is unknown. Other NMDA receptor antagonists have been shown to produce neurotoxic effects in animals.

Pharmacokinetics
Absorption

Following oral administration the bioavailability of methadone ranges between 36 to 100% and peak plasma concentrations are achieved between 1 to 7.5 hours. Dose proportionality of methadone pharmacokinetics is not known. However, after administration of daily oral doses ranging from 10 to 225 mg, the steady-state plasma concentrations ranged between 65 to 630 ng/mL and the peak concentrations ranged between 124 to 1255 ng/mL. Effect of food on the bioavailability of methadone has not been evaluated.

Distribution

Methadone is a lipophilic drug and the steady-state volume of distribution ranges between 1.0 to 8.0 L/kg. In plasma, methadone is predominantly bound to α-acid glycoprotein (85% to 90%). Methadone is secreted in saliva, breast milk, amniotic fluid and umbilical cord plasma.

Metabolism

Methadone is primarily metabolized by N-demethylation to an inactive metabolite, 2-ethylidene-1,5-dimethyl-3,3-diphenylpyrrolidene (EDDP). Cytochrome P450 enzymes, primarily CYP3A4, CYP2B6, and CYP2C19 and to a lesser extent CYP2C9 and CYP2D6, are responsible for conversion of methadone to EDDP and other inactive metabolites, which are excreted mainly in the urine.

Excretion

The elimination of methadone is mediated by extensive biotransformation, followed by renal and fecal excretion. Published reports indicate that after multiple dose administration the terminal half-life (T1/2) was highly variable and ranged between 8 to 59 hours in different studies. Since methadone is lipophilic, it has been known to persist in the liver and other tissues. The slow release from the liver and other tissues may prolong the duration of methadone action despite low plasma concentrations.

Pharmacokinetics in Special Populations
Pregnancy

The disposition of oral methadone has been studied in approximately 30 pregnant patients in 2nd and 3rd trimesters. Elimination of methadone was significantly changed in pregnancy. Total body clearance of methadone was increased in pregnant patients compared to the same patients postpartum or to non-pregnant opioid-dependent women. The terminal half-life of methadone is decreased during 2nd and 3rd trimesters. The decrease in plasma half-life and increased clearance of methadone resulting in lower methadone trough levels during pregnancy can lead to withdrawal symptoms in some pregnant patients. The dosage may need to be increased or the dosing interval decreased in pregnant patients receiving methadone. (See PRECAUTIONS: Pregnancy, Labor and Delivery, and DOSAGE AND ADMINISTRATION.)

Renal Impairment

Methadone pharmacokinetics have not been extensively evaluated in patients with renal insufficiency. Unmetabolized methadone and its metabolites are excreted in urine to a variable degree. Methadone is a basic (pKa=9.2) compound and the pH of the urinary tract can alter its disposition in plasma. Urine acidification has been shown to increase renal elimination of methadone. Forced diuresis, peritoneal dialysis, hemodialysis, or charcoal hemoperfusion have not been established as beneficial for increasing the elimination of methadone or its metabolites.

Hepatic Impairment

Methadone has not been extensively evaluated in patients with hepatic insufficiency. Methadone is metabolized by hepatic pathways, therefore patients with liver impairment may be at risk of accumulating methadone after multiple dosing.

Gender

The pharmacokinetics of methadone have not been evaluated for gender specificity.

Race

The pharmacokinetics of methadone have not been evaluated for race specificity.

Geriatric

The pharmacokinetics of methadone have not been evaluated in the geriatric population.

Pediatric

The pharmacokinetics of methadone have not been evaluated in the pediatric population.

Drug Interactions

(see PRECAUTIONS, Drug Interactions)

Methadone undergoes hepatic N-demethylation by cytochrome P-450 isoforms, principally CYP3A4, CYP2B6, CYP2C19, and to a lesser extent by CYP2C9 and CYP2D6. Coadministration of methadone with inducers of these enzymes may result in more rapid methadone metabolism, and potentially, decreased effects of methadone. Conversely, administration with CYP inhibitors may reduce metabolism and potentiate methadone’s effects. Pharmacokinetics of methadone may be unpredictable when coadministered with drugs that are known to both induce and inhibit CYP enzymes. Although antiretroviral drugs such as efavirenz, nelfinavir, nevirapine, ritonavir, lopinavir+ritonavir combination are known to inhibit some CYPs, they are shown to reduce the plasma levels of methadone, possibly due to their CYP induction activity. Therefore, drugs administered concomitantly with methadone should be evaluated for interaction potential; clinicians are advised to evaluate individual response to drug therapy before making a dosage adjustment.

INDICATIONS AND USAGE

1. For the treatment of moderate to severe pain not responsive to non-narcotic analgesics.
2. For detoxification treatment of opioid addiction (heroin or other morphine-like drugs).
3. For maintenance treatment of opioid addiction (heroin or other morphine-like drugs), in conjunction with appropriate social and medical services.

NOTE

Outpatient maintenance and outpatient detoxification treatment may be provided only by Opioid Treatment Programs (OTPs) certified by the Federal Substance Abuse and Mental Health Services Administration (SAMHSA) and registered by the Drug Enforcement Administration (DEA). This does not preclude the maintenance treatment of a patient with concurrent opioid addiction who is hospitalized for conditions other than opioid addiction and who requires temporary maintenance during the critical period of his/her stay, or of a patient whose enrollment has been verified in a program which has been certified for maintenance treatment with methadone.

CONTRAINDICATIONS

Methadone is contraindicated in patients with a known hypersensitivity to methadone hydrochloride or any other ingredient in Methadone Hydrochloride Tablets.

Methadone is contraindicated in any situation where opioids are contraindicated such as: patients with respiratory depression (in the absence of resuscitative equipment or in unmonitored settings), and in patients with acute bronchial asthma or hypercarbia.

Methadone is contraindicated in any patient who has or is suspected of having a paralytic ileus.

WARNINGS:

Respiratory Depression, Incomplete Cross-tolerance, and Iatrogenic Overdose
Respiratory depression is the chief hazard associated with methadone hydrochloride administration. Methadone's peak respiratory depressant effects typically occur later, and persist longer than its peak analgesic effects, particularly during the initial dosing period. These characteristics can contribute to cases of iatrogenic overdose, particularly during treatment initiation or dose titration.
Patients tolerant to other opioids may be incompletely tolerant to methadone. Incomplete cross-tolerance is of particular concern for patients tolerant to other mu-opioid agonists who are being converted to treatment with methadone, thus making determination of dosing during opioid treatment conversion complex. Deaths have been reported during conversion from chronic, high-dose treatment with other opioid agonists. Therefore, it is critical to understand the pharmacokinetics of methadone when converting patients from other opioids (see DOSAGE AND ADMINISTRATION, Table 1, for appropriate conversion schedules). A high degree of "opioid tolerance" does not eliminate the possibility of methadone overdose, iatrogenic or otherwise.
Respiratory depression is of particular concern in elderly or debilitated patients as well as in those suffering from conditions accompanied by hypoxia or hypercapnia when even moderate therapeutic doses may dangerously decrease pulmonary ventilation.
Methadone should be administered with extreme caution to patients with conditions accompanied by hypoxia, hypercapnia, or decreased respiratory reserve such as: asthma, chronic obstructive pulmonary disease or cor pulmonale, severe obesity, sleep apnea syndrome, myxedema, kyphoscoliosis, and CNS depression or coma. In these patients, even usual therapeutic doses of methadone may decrease respiratory drive while simultaneously increasing airway resistance to the point of apnea. Alternative, non-opioid analgesics should be considered, and methadone should be used at the lowest effective dose and only under careful medical supervision.
Cardiac Conduction Effects
Laboratory studies, both in vivo and in vitro, have demonstrated that methadone inhibits cardiac potassium channels and prolongs the QT interval. Cases of QT interval prolongation and serious arrhythmia (torsades de pointes) have been observed during treatment with methadone. These cases appear to be more commonly associated with, but not limited to, higher dose treatment (> 200 mg/day). Most cases involve patients being treated for pain with large, multiple daily doses of methadone, although cases have been reported in patients receiving doses commonly used for maintenance treatment of opioid addiction. In most of the cases seen at typical maintenance doses, concomitant medications and/or clinical conditions such as hypokalemia were noted as contributing factors. However, the evidence strongly suggests that methadone possesses the potential for adverse cardiac conduction effects in some patients.
Methadone should be administered with particular caution to patients already at risk for development of prolonged QT interval (e.g., cardiac hypertrophy, concomitant diuretic use, hypokalemia, hypomagnesemia). Careful monitoring is recommended when using methadone in patients with a history of cardiac conduction abnormalities, those taking medications affecting cardiac conduction, and in other cases where history or physical exam suggest an increased risk of dysrhythmia. QT prolongation has also been reported in patients with no prior cardiac history who have received high doses of methadone. Patients developing QT prolongation while on methadone treatment should be evaluated for the presence of modifiable risk factors, such as concomitant medications with cardiac effects, drugs which might cause electrolyte abnormalities, and drugs which might act as inhibitors of methadone metabolism. For use of methadone to treat pain, the risk of QT prolongation and development of dysrhythmias should be weighed against the benefit of adequate pain management and the availability of alternative therapies.
Methadone treatment for analgesic therapy in patients with acute or chronic pain should only be initiated if the potential analgesic or palliative care benefit of treatment with methadone has been considered to outweigh the risk of QT prolongation that has been reported with high doses of methadone.
The use of methadone in patients already known to have a prolonged QT interval has not been systematically studied.
In using methadone an individualized benefit to risk assessment should be carried out and should include evaluation of patient presentation and complete medical history. For patients judged to be at risk, careful monitoring of cardiovascular status, including QT prolongation and dysrhythmias and those described previously should be performed.
Misuse, Abuse, and Diversion of Opioids
Methadone is a mu-agonist opioid with an abuse liability similar to that of morphine and is a Schedule II controlled substance. Methadone, like morphine and other opioids used for analgesia, has the potential for being abused and is subject to criminal diversion.
Methadone can be abused in a manner similar to other opioid agonists, legal or illicit. This should be considered when prescribing or dispensing methadone in situations where the clinician is concerned about an increased risk of misuse, abuse, or diversion.
Concerns about abuse, addiction, and diversion should not prevent the proper management of pain.
Healthcare professionals should contact their State Professional Licensing Board, or State Controlled Substances Authority for information on how to prevent and detect abuse or diversion of this product.
Interactions with other CNS Depressants
Patients receiving other opioid analgesics, general anesthetics, phenothiazines, other tranquilizers, sedatives, hypnotics or other CNS depressants (including alcohol) concomitantly with methadone may experience respiratory depression, hypotension, profound sedation, or coma (see PRECAUTIONS).
Interactions with Alcohol and Drugs of Abuse
Methadone may be expected to have additive effects when used in conjunction with alcohol, other opioids, or illicit drugs that cause central nervous system depression. Deaths associated with illicit use of methadone frequently have involved concomitant benzodiazepine abuse.
Head Injury and Increased Intracranial Pressure
The respiratory depressant effects of opioids and their capacity to elevate cerebrospinal-fluid pressure may be markedly exaggerated in the presence of head injury, other intracranial lesions or a pre-existing increase in intracranial pressure. Furthermore, opioids produce effects which may obscure the clinical course of patients with head injuries. In such patients, methadone must be used with caution, and only if it is deemed essential.
Acute Abdominal Conditions
The administration of opioids may obscure the diagnosis or clinical course of patients with acute abdominal conditions.
Hypotensive Effect
The administration of methadone may result in severe hypotension in patients whose ability to maintain normal blood pressure is compromised (e.g., severe volume depletion).

DRUG ABUSE AND DEPENDENCE

Methadone is a mu-agonist opioid with an abuse liability similar to other opioid agonists and is a Schedule II controlled substance. Methadone and other opioids used in analgesia can be abused and are subject to criminal diversion.

Abuse of methadone poses a risk of overdose and death. This risk is increased with concurrent abuse of methadone with alcohol and other substances. In addition, parenteral drug abuse is commonly associated with transmission of infectious diseases such as hepatitis and HIV.

Drug addiction is characterized by compulsive use, use for non-medical purposes, and continued use despite harm or risk of harm. Drug addiction is a treatable disease, utilizing a multi-disciplinary approach, but relapse is common.

“Drug-seeking” behavior is very common in addicts and drug abusers. Drug-seeking tactics include emergency calls or visits near the end of office hours, refusal to undergo appropriate examination, testing or referral, repeated claims of lost prescriptions, tampering with prescriptions and reluctance to provide prior medical records or contact information for other treating physician(s). “Doctor shopping” (visiting multiple prescribers) to obtain additional prescriptions is common among drug abusers and people suffering from untreated addiction. However, it should be important to note that preoccupation with achieving adequate pain relief can be appropriate behavior in a patient with poor pain control.

Physical Dependence and Tolerance

Abuse and addiction are separate and distinct from physical dependence and tolerance. Physicians should be aware that addiction may not be accompanied by concurrent tolerance and symptoms of physical dependence in all addicts. In addition, abuse of opioids can occur in the absence of true addiction and is characterized by misuse for non-medical purposes, often in combination with other psychoactive substances. Methadone, like other opioids, has been diverted for non-medical use. Careful record-keeping of prescribing information, including quantity, frequency, and renewal requests is strongly advised.

Proper assessment of the patient, proper prescribing practices, periodic re-evaluation of therapy, and proper dispensing and storage are appropriate measures that help to limit abuse of opioid drugs.

Infants born to mothers physically dependent on opioids may also be physically dependent and may exhibit respiratory difficulties and withdrawal symptoms (see PRECAUTIONS; Pregnancy, Labor and Delivery).

PRECAUTIONS

General

When treating pain, methadone given on a fixed-dose schedule may have a narrow therapeutic index in certain patient populations, especially when combined with other drugs, and should be reserved for cases where the benefits of opioid analgesia with methadone outweigh the known potential risks of cardiac conduction abnormalities, respiratory depression, altered mental states and postural hypotension. Methadone should be used with caution in elderly and debilitated patients; patients who are known to be sensitive to central nervous system depressants, such as those with cardiovascular, pulmonary, renal, or hepatic disease; and in patients with comorbid conditions or concomitant medications which may predispose to dysrhythmia.

Selection of patients for treatment with methadone should be governed by the same principles that apply to the use of other opioids (see INDICATIONS AND USAGE). Physicians should individualize treatment in every case (see DOSAGE AND ADMINISTRATION), taking into account the high degree of interpatient variability in response to and metabolism of methadone

Drug Interactions

In vitro results suggest that methadone undergoes hepatic N-demethylation by cytochrome P450 enzymes, principally CYP3A4, CYP2B6, CYP2C19 and to a lesser extent by CYP2C9 and CYP2D6. Coadministration of methadone with CYP inducers of these enzymes may result in a more rapid metabolism and potential for decreased effects of methadone, whereas administration with CYP inhibitors may reduce metabolism and potentiate methadone’s effects. Although antiretroviral drugs such as efavirenz, nelfinavir, nevirapine, ritonavir, lopinavir+ritonavir combination are known to inhibit CYPs, they are shown to reduce the plasma levels of methadone, possibly due to their CYP induction activity. Therefore, drugs administered concomitantly with methadone should be evaluated for interaction potential; clinicians are advised to evaluate individual response to drug therapy.

Opioid Antagonists, Mixed Agonist/Antagonists, and Partial Agonists

As with other mu-agonists, patients maintained on methadone may experience withdrawal symptoms when given opioid antagonists, mixed agonist/antagonists, and partial agonists. Examples of such agents are naloxone, naltrexone, pentazocine, nalbuphine, butorphanol, and buprenorphine.

Anti-retroviral Agents
Abacavir, amprenavir, efavirenz, nelfinavir, nevirapine, ritonavir, lopinavir+ritonavir combination

Coadministration of these anti-retroviral agents resulted in increased clearance or decreased plasma levels of methadone. Methadone-maintained patients beginning treatment with these antiretroviral drugs should be monitored for evidence of withdrawal effects and methadone dose should be adjusted accordingly.

Didanosine and Stavudine

Experimental evidence demonstrated that methadone decreased the AUC and peak levels for didanosine and stavudine, with a more significant decrease for didanosine. Methadone disposition was not substantially altered.

Zidovudine

Experimental evidence demonstrated that methadone increased the area under the concentration-time curve (AUC) of zidovudine which could result in toxic effects.

Cytochrome P450 Inducers

Methadone-maintained patients beginning treatment with CYP3A4 inducers should be monitored for evidence of withdrawal effects and methadone dose should be adjusted accordingly. The following drug interactions were reported following coadministration of methadone with inducers of cytochrome P450 enzymes:

Rifampin

In patients well-stabilized on methadone, concomitant administration of rifampin resulted in a marked reduction in serum methadone levels and a concurrent appearance of withdrawal symptoms.

Phenytoin

In a pharmacokinetic study with patients on methadone maintenance therapy, phenytoin administration (250 mg b.i.d. initially for 1 day followed by 300 mg QD for 3 to 4 days) resulted in an approximately 50% reduction in methadone exposure and withdrawal symptoms occurred concurrently. Upon discontinuation of phenytoin, the incidence of withdrawal symptoms decreased and methadone exposure increased to a level comparable to that prior to phenytoin administration.

St. John’s Wort, Phenobarbital, Carbamazepine

Administration of methadone along with other CYP3A4 inducers may result in withdrawal symptoms.

Cytochrome P450 Inhibitors

Since the metabolism of methadone is mediated primarily by CYP3A4 isozyme, coadministration of drugs that inhibit CYP3A4 activity may cause decreased clearance of methadone. The expected clinical results would be increased or prolonged opioid effects. Thus, methadone-treated patients coadministered strong inhibitors of CYP3A4, such as azole antifungal agents (e.g., ketoconazole) and macrolide antibiotics (e.g., erythromycin), with methadone should be carefully monitored and dosage adjustment should be undertaken if warranted. Some selective serotonin reuptake inhibitors (SSRIs) (e.g., sertraline, fluvoxamine) may increase methadone plasma levels upon coadministration with methadone and result in increased opiate effects and/or toxicity.

Voriconazole

Repeat dose administration of oral voriconazole (400mg Q12h for 1 day, then 200mg Q12h for 4 days) increased the Cmax and AUC of (R)-methadone by 31% and 47%, respectively, in subjects receiving a methadone maintenance dose (30 to 100 mg QD). The Cmax and AUC of (S)-methadone increased by 65% and 103%, respectively. Increased plasma concentrations of methadone have been associated with toxicity including QT prolongation. Frequent monitoring for adverse events and toxicity related to methadone is recommended during coadministration. Dose reduction of methadone may be needed.

Others
Monoamine Oxidase (MAO) Inhibitors

Therapeutic doses of meperidine have precipitated severe reactions in patients concurrently receiving monoamine oxidase inhibitors or those who have received such agents within 14 days. Similar reactions thus far have not been reported with methadone. However, if the use of methadone is necessary in such patients, a sensitivity test should be performed in which repeated small, incremental doses of methadone are administered over the course of several hours while the patient's condition and vital signs are under careful observation.

Desipramine

Blood levels of desipramine have increased with concurrent methadone administration.

Potentially Arrhythmogenic Agents

Extreme caution is necessary when any drug known to have the potential to prolong the QT interval is prescribed in conjunction with methadone. Pharmacodynamic interactions may occur with concomitant use of methadone and potentially arrhythmogenic agents such as class I and III antiarrhythmics, some neuroleptics and tricyclic antidepressants, and calcium channel blockers.

Caution should also be exercised when prescribing methadone concomitantly with drugs capable of inducing electrolyte disturbances (hypomagnesemia, hypokalemia) that may prolong the QT interval. These drugs include diuretics, laxatives, and, in rare cases, mineralocorticoid hormones.

Interactions with Alcohol and Drugs of Abuse

Methadone may be expected to have additive effects when used in conjunction with alcohol, other opioids or CNS depressants, or with illicit drugs that cause central nervous system depression. Deaths have been reported when methadone has been abused in conjunction with benzodiazepines.

Anxiety

Since methadone as used by tolerant patients at a constant maintenance dosage does not act as a tranquilizer, patients who are maintained on this drug will react to life problems and stresses with the same symptoms of anxiety as do other individuals. The physician should not confuse such symptoms with those of narcotic abstinence and should not attempt to treat anxiety by increasing the dose of methadone. The action of methadone in maintenance treatment is limited to the control of narcotic withdrawal symptoms and is ineffective for relief of general anxiety.

Acute Pain

Maintenance patients on a stable dose of methadone who experience physical trauma, postoperative pain or other acute pain cannot be expected to derive analgesia from their existing dose of methadone. Such patients should be administered analgesics, including opioids, in doses that would otherwise be indicated for non-methadone-treated patients with similar painful conditions. Due to the opioid tolerance induced by methadone, when opioids are required for management of acute pain in methadone patients, somewhat higher and/or more frequent doses will often be required than would be the case for non-tolerant patients.

Risk of Relapse in Patients on Methadone Maintenance Treatment of Opioid Addiction

Abrupt opioid discontinuation can lead to development of opioid withdrawal symptoms (see PRECAUTIONS). Presentation of these symptoms have been associated with an increased risk of susceptible patients to relapse to illicit drug use and should be considered when assessing the risks and benefit of methadone use.

Tolerance and Physical Dependence

Tolerance is the need for increasing doses of opioids to maintain a defined effect such as analgesia (in the absence of disease progression or other external factors). Physical dependence is manifested by withdrawal symptoms after abrupt discontinuation of a drug or upon administration of an antagonist. Physical dependence and/or tolerance are not unusual during chronic opioid therapy.

If methadone is abruptly discontinued in a physically dependent patient, an abstinence syndrome may occur. The opioid abstinence or withdrawal syndrome is characterized by some or all of the following: restlessness, lacrimation, rhinorrhea, yawning, perspiration, chills, myalgia, and mydriasis. Other symptoms also may develop, including irritability, anxiety, backache, joint pain, weakness, abdominal cramps, insomnia, nausea, anorexia, vomiting, diarrhea, or increased blood pressure, respiratory rate, or heart rate.

In general, chronically administered methadone should not be abruptly discontinued.

Special-Risk Patients

Methadone should be given with caution and the initial dose reduced in certain patients, such as the elderly and debilitated and those with severe impairment of hepatic or renal function, hypothyroidism, Addison’s disease, prostatic hypertrophy, or urethral stricture. The usual precautions appropriate to the use of parenteral opioids should be observed and the possibility of respiratory depression should always be kept in mind.

Information for Patients

- Patients should be cautioned that methadone, like all opioids, may impair the mental and/or physical abilities required for the performance of potentially hazardous tasks such as driving or operating machinery.

- Patients should be cautioned that methadone, like other opioids, may produce orthostatic hypotension in ambulatory patients.

- Patients should be cautioned that alcohol and other CNS depressants may produce an additive CNS depression when taken with this product and should be avoided.

- Patients should be instructed to seek medical attention immediately if they experience symptoms suggestive of an arrhythmia (such as palpitations, dizziness, lightheadedness, or syncope) when taking methadone.

- Patients initiating treatment with methadone for opioid dependence should be reassured that the dose of methadone will “hold” for longer periods of time as treatment progresses.

- Patients seeking to discontinue methadone maintenance treatment of opioid dependence should be apprised of the high risk of relapse to illicit drug use associated with discontinuation of methadone maintenance treatment.

- Patients should be instructed to keep methadone in a secure place out of the reach of children and other household members. Accidental or deliberate ingestion by a child may cause respiratory depression that can result in death. Patients and their caregivers should be advised to discard unused methadone in such a way that individuals other than the patient for whom it was originally prescribed will not come in contact with the drug.

Carcinogenesis, Mutagenesis, Impairment of Fertility
Carcinogenesis

The results of carcinogenicity assessment in B6C2F1 mice and Fischer 344 rats following dietary administration of two doses of methadone HCl have been published. Mice consumed 15 mg/kg/day or 60 mg/kg/day methadone for two years. These doses were approximately 0.6 and 2.5 times a human daily oral dose of 120 mg/day on a body surface area basis (mg/m^2). There was a significant increase in pituitary adenomas in female mice treated with 15 mg/kg/day but not with 60 mg/kg/day. Under the conditions of the assay, there was no clear evidence for a treatment-related increase in the incidence of neoplasms in male rats. Due to decreased food consumption in males at the high dose, male rats consumed 16 mg/kg/day and 28 mg/kg/day of methadone for two years. These doses were approximately 1.3 and 2.3 times a human daily oral dose of 120 mg/day, based on body surface area comparison. In contrast, female rats consumed 46 mg/kg/day or 88 mg/kg/day for two years. These doses were approximately 3.7 and 7.1 times a human daily oral dose of 120 mg/day, based on body surface area comparison. Under the conditions of the assay, there was no clear evidence for a treatment-related increase in the incidence of neoplasms in either male or female rats.

Mutagenesis

There are several published reports on the potential genetic toxicity of methadone. Methadone tested negative in tests for chromosome breakage and disjunction and sex-linked recessive lethal gene mutations in germ cells of Drosophila using feeding and injection procedures. In contrast, methadone tested positive in the in vivo mouse dominant lethal assay and the in vivo mammalian spermatogonial chromosome aberration test. Additionally, methadone tested positive in the E. coli DNA repair system and Neurospora crassa and mouse lymphoma forward mutation assays.

Fertility

Reproductive function in human males may be decreased by methadone treatment. Reductions in ejaculate volume and seminal vesicle and prostate secretions have been reported in methadone-treated individuals. In addition, reductions in serum testosterone levels and sperm motility, and abnormalities in sperm morphology have been reported. Published animal studies provide additional data indicating that methadone treatment of males can alter reproductive function. Methadone produces a significant regression of sex accessory organs and testes of male mice and rats. Additional data have been published indicating that methadone treatment of male rats (once a day for three consecutive days) increased embryolethality and neonatal mortality. Examination of uterine contents of methadone-naive female mice bred to methadone-treated mice indicated that methadone treatment produced an increase in the rate of preimplantation deaths in all post-meiotic states.

Pregnancy
Teratogenic Effects
Pregnancy Category C

There are no controlled studies of methadone use in pregnant women that can be used to establish safety. However, an expert review of published data on experiences with methadone use during pregnancy by the Teratogen Information System (TERIS) concluded that maternal use of methadone during pregnancy as part of a supervised, therapeutic regimen is unlikely to pose a substantial teratogenic risk (quantity and quality of data assessed as “limited to fair”). However, the data are insufficient to state that there is no risk (TERIS, last reviewed October, 2002). Pregnant women involved in methadone maintenance programs have been reported to have significantly improved prenatal care leading to significantly reduced incidence of obstetric and fetal complications and neonatal morbidity and mortality when compared to women using illicit drugs. Several factors complicate the interpretation of investigations of the children of women who take methadone during pregnancy. These include the maternal use of illicit drugs, other maternal factors such as nutrition, infection, and psychosocial circumstances, limited information regarding dose and duration of methadone use during pregnancy, and the fact that most maternal exposure appears to occur after the first trimester of pregnancy. In addition, reported studies generally compare the benefit of methadone to the risk of untreated addiction to illicit drugs; the relevance of these findings to pain patients prescribed methadone during pregnancy is unclear.

Methadone has been detected in amniotic fluid and cord plasma at concentrations proportional to maternal plasma and in newborn urine at lower concentrations than corresponding maternal urine.

A retrospective series of 101 pregnant, opiate-dependent women who underwent inpatient opiate detoxification with methadone did not demonstrate any increased risk of miscarriage in the 2nd trimester or premature delivery in the 3rd trimester.

Several studies have suggested that infants born to narcotic-addicted women treated with methadone during all or part of pregnancy have been found to have decreased fetal growth with reduced birth weight, length, and/or head circumference compared to controls. This growth deficit does not appear to persist into later childhood. However, children born to women treated with methadone during pregnancy have been shown to demonstrate mild but persistent deficits in performance on psychometric and behavioral tests.

Additional information on the potential risks of methadone may be derived from animal data. Methadone does not appear to be teratogenic in the rat or rabbit models. However, following large doses, methadone produced teratogenic effects in the guinea pig, hamster and mouse. One published study in pregnant hamsters indicated that a single subcutaneous dose of methadone ranging from 31 to 185 mg/kg (the 31 mg/kg dose is approximately 2 times a human daily oral dose of 120 mg/day on a mg/m^2 basis) on day 8 of gestation resulted in a decrease in the number of fetuses per litter and an increase in the percentage of fetuses exhibiting congenital malformations described as exencephaly, cranioschisis, and “various other lesions.” The majority of the doses tested also resulted in maternal death. In another study, a single subcutaneous dose of 22 to 24 mg/kg methadone (estimated exposure was approximately equivalent to a human daily oral dose of 120 mg/day on a mg/m^2 basis) administered on day 9 of gestation in mice also produced exencephaly in 11% of the embryos. However, no effects were reported in rats and rabbits at oral doses up to 40 mg/kg (estimated exposure was approximately 3 and 6 times, respectively, a human daily oral dose of 120 mg/day on a mg/m^2 basis) administered during days 6 to 15 and 6 to 18, respectively.

Nonteratogenetic Effects

Babies born to mothers who have been taking opioids regularly prior to delivery may be physically dependent. Onset of withdrawal symptoms in infants is usually in the first days after birth. Withdrawal signs in the newborn include irritability and excessive crying, tremors, hyperactive reflexes, increased respiratory rate, increased stools, sneezing, yawning, vomiting, and fever. The intensity of the syndrome does not always correlate with the maternal dose or the duration of maternal exposure. The duration of the withdrawal signs may vary from a few days to weeks or even months. There is no consensus on the appropriate management of infant withdrawal.

There are conflicting reports on whether SIDS occurs with an increased incidence in infants born to women treated with methadone during pregnancy.

Abnormal fetal nonstress tests (NSTs) have been reported to occur more frequently when the test is performed 1 to 2 hours after a maintenance dose of methadone in late pregnancy compared to controls.

Published animal data have reported increased neonatal mortality in the offspring of male rodents that were treated with methadone prior to mating. In these studies, the female rodents were not treated with methadone, indicating paternally-mediated developmental toxicity. Specifically, methadone administered to the male rat prior to mating with methadone-naïve females resulted in decreased weight gain in progeny after weaning. The male progeny demonstrated reduced thymus weights, whereas the female progeny demonstrated increased adrenal weights. Further, behavioral testing of these male and female progeny revealed significant differences in behavioral tests compared to control animals, suggesting that paternal methadone exposure can produce physiological and behavioral changes in progeny in this model. Other animal studies have reported that perinatal exposure to opioids including methadone alters neuronal development and behavior in the offspring. Perinatal methadone exposure in rats has been linked to alterations in learning ability, motor activity, thermal regulation, nociceptive responses and sensitivity to drugs. Additional animal data demonstrates evidence for neurochemical changes in the brains of methadone-treated offspring, including changes to the cholinergic, dopaminergic, noradrenergic and serotonergic systems. Additional studies demonstrated that methadone treatment of male rats for 21 to 32 days prior to mating with methadone-naïve females did not produce any adverse effects, suggesting that prolonged methadone treatment of the male rat resulted in tolerance to the developmental toxicities noted in the progeny. Mechanistic studies in this rat model suggest that the developmental effects of “paternal” methadone on the progeny appear to be due to decreased testosterone production. These animal data mirror the reported clinical findings of decreased testosterone levels in human males on methadone maintenance therapy for opioid addiction and in males receiving chronic intraspinal opioids.

Clinical Pharmacology for Pregnancy

Pregnant women appear to have significantly lower trough plasma methadone concentrations, increased plasma methadone clearance, and shorter methadone half-life than after delivery. Dosage adjustment using higher doses or administering the daily dose in divided doses may be necessary in pregnant women treated with methadone. [See CLINICAL PHARMACOLOGY and DOSAGE AND ADMINISTRATION].

Methadone should be used during pregnancy only if the potential benefit justifies the potential risk to the fetus.

Labor and Delivery

As with all opioids, administration of this product to the mother shortly before delivery may result in some degree of respiratory depression in the newborn, especially if higher doses are used. Methadone is not recommended for obstetric analgesia because its long duration of action increases the probability of respiratory depression in the newborn. Narcotics with mixed agonist-antagonist properties should not be used for pain control during labor in patients chronically treated with methadone as they may precipitate acute withdrawal.

Nursing Mothers

Methadone is secreted into human milk. The safety of breastfeeding while taking oral methadone is controversial. At maternal oral doses of 10 to 80 mg/day, methadone concentrations from 50 to 570 mcg/L in milk have been reported, which, in the majority of samples, were lower than maternal serum drug concentrations at steady state. Peak methadone levels in milk occur approximately 4 to 5 hours after an oral dose. Based on an average milk consumption of 150 mL/kg/day, an infant would consume approximately 17.4 mcg/kg/day which is approximately 2 to 3% of the oral maternal dose. Methadone has been detected in very low plasma concentrations in some infants whose mothers were taking methadone. Women on high dose methadone maintenance, who are already breast feeding, should be counseled to wean breast-feeding gradually in order to prevent neonatal abstinence syndrome.

Methadone-treated mothers considering nursing an opioid-naïve infant should be counseled regarding the presence of methadone in breast milk.

Because of the potential for serious adverse reactions in nursing infants from methadone, a decision should be made whether to discontinue nursing or to discontinue the drug, taking into account the importance of the drug to the mother. In patients being treated for opioid dependence, this should include weighing the risk of methadone against the risk of maternal illicit drug use.

Pediatric Use

Safety and effectiveness in pediatric patients below the age of 18 years have not been established.

Accidental or deliberate ingestion by a child may cause respiratory depression that can result in death. Patients and caregivers should be instructed to keep methadone in a secure place out of the reach of children and to discard unused methadone in such a way that individuals other than the patient for whom it was originally prescribed will not come in contact with the drug.

Geriatric Use

Clinical studies of methadone did not include sufficient numbers of subjects aged 65 and over to determine whether they respond differently compared to younger subjects. Other reported clinical experience has not identified differences in responses between elderly and younger patients. In general, dose selection for elderly patients should be cautious, usually starting at the low end of the dosing range, reflecting the greater frequency of decreased hepatic, renal, or cardiac function and of concomitant disease or other drug therapy.

Renal Impairment

The use of methadone has not been extensively evaluated in patients with renal insufficiency.

Hepatic Impairment

The use of methadone has not been extensively evaluated in patients with hepatic insufficiency. Methadone is metabolized in the liver and patients with liver impairment may be at risk of accumulating methadone after multiple dosing.

Gender

The use of methadone has not been evaluated for gender specificity.

ADVERSE REACTIONS

Heroin Withdrawal

During the induction phase of methadone maintenance treatment, patients are being withdrawn from heroin and may therefore show typical withdrawal symptoms, which should be differentiated from methadone-induced side effects. They may exhibit some or all of the following signs and symptoms associated with acute withdrawal from heroin or other opiates: lacrimation, rhinorrhea, sneezing, yawning, excessive perspiration, goose-flesh, fever, chilliness alternating with flushing, restlessness, irritability, weakness, anxiety, depression, dilated pupils, tremors, tachycardia, abdominal cramps, body aches, involuntary twitching and kicking movements, anorexia, nausea, vomiting, diarrhea, intestinal spasms, and weight loss.

Initial Administration

The initial methadone dose should be carefully titrated to the individual. Too rapid titration for the patient’s sensitivity is more likely to produce adverse effects.

The major hazards of methadone are respiratory depression and, to a lesser degree, systemic hypotension. Respiratory arrest, shock, cardiac arrest, and death have occurred.

The most frequently observed adverse reactions include lightheadedness, dizziness, sedation, nausea, vomiting, and sweating. These effects seem to be more prominent in ambulatory patients and in those who are not suffering severe pain. In such individuals, lower doses are advisable.

Other adverse reactions include the following (listed alphabetically under each subsection):

Body as a Whole

asthenia (weakness), edema, headache

Cardiovascular

arrhythmias, bigeminal rhythms, bradycardia, cardiomyopathy, ECG abnormalities, extrasystoles, flushing, heart failure, hypotension, palpitations, phlebitis, QT interval prolongation, syncope, T-wave inversion, tachycardia, torsade de pointes, ventricular fibrillation, ventricular tachycardia

Digestive

abdominal pain, anorexia, biliary tract spasm, constipation, dry mouth, glossitis

Hematologic and Lymphatic

reversible thrombocytopenia has been described in opioid addicts with chronic hepatitis

Metabolic and Nutritional

hypokalemia, hypomagnesemia, weight gain

Nervous

agitation, confusion, disorientation, dysphoria, euphoria, insomnia, seizures

Respiratory

pulmonary edema, respiratory depression

Skin and Appendages

pruritis, urticaria, other skin rashes, and rarely, hemorrhagic urticaria

Special Senses

hallucinations, visual disturbances

Urogenital

amenorrhea, antidiuretic effect, reduced libido and/or potency, urinary retention or hesitancy

Maintenance on a Stabilized Dose

During prolonged administration of methadone, as in a methadone maintenance treatment program, there is usually a gradual, yet progressive, disappearance of side effects over a period of several weeks. However, constipation and sweating often persist.

DRUG ABUSE AND DEPENDENCE

Methadone is a mu-agonist opioid with an abuse liability similar to other opioid agonists and is a Schedule II controlled substance. Methadone and other opioids used in analgesia have the potential for being abused and are subject to criminal diversion.

Abuse

Drug addiction is characterized by compulsive use, use for non-medical purposes, and continued use despite harm or risk of harm. Drug addiction is a treatable disease, utilizing a multi-disciplinary approach, but relapse is common.

“Drug-seeking” behavior is very common in addicts and drug abusers. Drug-seeking tactics include emergency calls or visits near the end of office hours, refusal to undergo appropriate examination, testing or referral, repeated claims of lost prescriptions, tampering with prescriptions and reluctance to provide prior medical records or contact information for other treating physician(s). “Doctor shopping” (visiting multiple prescribers) to obtain additional prescriptions is common among drug abusers and people suffering from untreated addiction. However, it should be important to note that preoccupation with achieving adequate pain relief can be appropriate behavior in a patient with poor pain control.

Physical Dependence and Tolerance

Abuse and addiction are separate and distinct from physical dependence and tolerance. Physicians should be aware that addiction may not be accompanied by concurrent tolerance and symptoms of physical dependence in all addicts. In addition, abuse of opioids can occur in the absence of true addiction and is characterized by misuse for non-medical purposes, often in combination with other psychoactive substances. Methadone, like other opioids, has been diverted for non-medical use. Careful record-keeping of prescribing information, including quantity, frequency, and renewal requests is strongly advised.

Proper assessment of the patient, proper prescribing practices, periodic re-evaluation of therapy, and proper dispensing and storage are appropriate measures that help to limit abuse of opioid drugs.

Infants born to mothers physically dependent on opioids may also be physically dependent and may exhibit respiratory difficulties and withdrawal symptoms (See PRECAUTIONS; Pregnancy, Labor and Delivery).

OVERDOSAGE

Signs and Symptoms

Serious overdosage of methadone is characterized by respiratory depression (a decrease in respiratory rate and/or tidal volume, Cheyne-Stokes respiration, cyanosis), extreme somnolence progressing to stupor or coma, maximally constricted pupils, skeletal-muscle flaccidity, cold and clammy skin, and sometimes, bradycardia and hypotension. In severe overdosage, particularly by the intravenous route, apnea, circulatory collapse, cardiac arrest, and death may occur.

Treatment

Primary attention should be given to the reestablishment of adequate respiratory exchange through provision of a patent airway and institution of assisted or controlled ventilation. If a non-tolerant person, takes a large dose of methadone, effective opioid antagonists are available to counteract the potentially lethal respiratory depression. The physician must remember, however, that methadone is a long-acting depressant (36 to 48 hours), whereas opioid antagonists act for much shorter periods (one to three hours). The patient must, therefore, be monitored continuously for recurrence of respiratory depression and may need to be treated repeatedly with the narcotic antagonist. If the diagnosis is correct and respiratory depression is due only to overdosage of methadone, the use of other respiratory stimulants is not indicated.

Opioid antagonists should not be administered in the absence of clinically significant respiratory or cardiovascular depression. In an individual physically dependent on opioids, the administration of the usual dose of an opioid antagonist may precipitate an acute withdrawal syndrome. The severity of this syndrome will depend on the degree of physical dependence and the dose of the antagonist administered. If antagonists must be used to treat serious respiratory depression in the physically dependent patient, the antagonist should be administered with extreme care and by titration with smaller than usual doses of the antagonist.

Intravenously administered naloxone or nalmefene may be used to reverse signs of intoxication. Because of the relatively short half-life of naloxone as compared with methadone, repeated injections may be required until the status of the patient remains satisfactory. Naloxone may also be administered by continuous intravenous infusion.

Oxygen, intravenous fluids, vasopressors, and other supportive measures should be employed as indicated.

DOSAGE AND ADMINISTRATION

Methadone differs from many other opioid agonists in several important ways. Methadone's pharmacokinetic properties, coupled with high interpatient variability in its absorption, metabolism, and relative analgesic potency, necessitate a cautious and highly individualized approach to prescribing. Particular vigilance is necessary during treatment initiation, during conversion from one opioid to another, and during dose titration.

While methadone’s duration of analgesic action (typically 4 to 8 hours) in the setting of single-dose studies approximates that of morphine, methadone’s plasma elimination half-life is substantially longer than that of morphine (typically 8 to 59 hours vs. 1 to 5 hours). Methadone's peak respiratory depressant effects typically occur later, and persist longer than its peak analgesic effects. Also, with repeated dosing, methadone may be retained in the liver and then slowly released, prolonging the duration of action despite low plasma concentrations. For these reasons, steady-state plasma concentrations, and full analgesic effects, are usually not attained until 3 to 5 days of dosing. Additionally, incomplete cross-tolerance between mu-opioid agonists makes determination of dosing during opioid conversion complex.

The complexities associated with methadone dosing can contribute to cases of iatrogenic overdose, particularly during treatment initiation and dose titration. A high degree of "opioid tolerance" does not eliminate thepossibility of methadone overdose, iatrogenic or otherwise. Deaths have been reported during conversion to methadone from chronic, high-dose treatment with other opioid agonists and during initiation of methadone treatment of addiction in subjects previously abusing high doses of other agonists.

Treatment of Pain

Optimal methadone initiation and dose titration strategies for the treatment of pain have not been determined. Published equianalgesic conversion ratios between methadone and other opioids are imprecise, providing at best, only population averages that cannot be applied consistently to all patients. It should be noted that many commonly cited equianalgesia tables only present relative analgesic potencies of single opioid doses in non-tolerant patients, thus greatly underestimating methadone’s analgesic potency, and its potential for adverse effects in repeated-dose settings. Regardless of the dose determination strategy employed, methadone is most safely initiated and titrated using small initial doses and gradual dose adjustments.

As with all opioid drugs, it is necessary to adjust the dosing regimen for each patient individually, taking into account the patient’s prior analgesic treatment experience. The following dosing recommendations should only be considered as suggested approaches to what is actually a series of clinical decisions over time in the management of the pain of each individual patient. Prescribers should always follow appropriate pain management principles of careful assessment and ongoing monitoring.

In the selection of an initial dose of Methadone Hydrochloride Tablets, attention should be given to the following:

1. The total daily dose, potency and specific characteristics of the opioid the patient had been taking previously, if any;
2. The relative potency estimate used to calculate an equianalgesic starting methadone dose, in particular, whether it is intended for use in acute or chronic methadone dosing;
3. The patient’s degree of opioid tolerance;
4. The age, general condition and medical status of the patient;
5. Concurrent medications, particularly other CNS and respiratory depressants;
6. The type, severity and expected duration of the patient’s pain;
7. The acceptable balance between pain control and adverse side effects.

Initiation of Therapy in Opioid Non-Tolerant Patients

When oral methadone is used as the first analgesic in patients who are not already being treated with, and tolerant to, opioids, the usual oral methadone starting dose is 2.5 mg to 10 mg every 8 to 12 hours, slowly titrated to effect. More frequent administration may be required during methadone initiation in order to maintain adequate analgesia, and extreme caution is necessary to avoid overdosage, taking into account methadone’s long elimination half-life.

Conversion from Parenteral Methadone to Oral Methadone

Conversion from parenteral methadone to oral methadone should initially use a 1:2 dose ratio (e.g., 5 mg parenteral methadone to 10 mg oral methadone).

Switching Patients to Methadone from other Chronic Opioids

Switching a patient from another chronically administered opioid to methadone requires caution due to the uncertainty of dose conversion ratios and incomplete cross-tolerance. Deaths have occurred in opioid tolerant patients during conversion to methadone.

Conversion ratios in many commonly used equianalgesic dosing tables do not apply in the setting of repeated methadone dosing. Although with single-dose administration the onset and duration of analgesic action, as well as the analgesic potency of methadone and morphine, are similar methadone’s potency increases over time with repeated dosing. Furthermore, the conversion ratio between methadone and other opiates varies dramatically depending on baseline opiate (morphine equivalent) use as shown in the table below.

The dose conversion scheme below is derived from various consensus guidelines for converting chronic pain patients to methadone from morphine. Clinicians should consult published conversion guidelines to determine the equivalent morphine dose for patients converting from other opioids.

Table 1. Oral Morphine to Oral Methadone Conversion for Chronic Administration

Total Daily Baseline Oral Morphine Dose |  | Estimated Daily Oral Methadone Requirement as Percent of Total Daily Morphine Dose
less than 100mg |  | 20 % to 30 %
100 mg to300 mg |  | 10 % to 20 %
300 mg to600 mg |  | 8 % to 12 %
600 mg to1000 mg |  | 5 % to 10 %
> 1000 mg |  | less than 5 %

The total daily methadone dose derived from the table above may then be divided to reflect the intended dosing schedule (i.e., for administration every 8 hours, divide total daily methadone dose by 3).

Note: Equianalgesic methadone dosing varies not only between patients, but also within the same patient, depending on baseline morphine (or other opioid) dose. Table 1 has been included in order to illustrate this concept and to provide a safe starting point for opioid conversion. Methadone dosing should not be based solely on these tables. Methadone conversion and dose titration methods should always be individualized to account for the patient’s prior opioid exposure, general medical condition, concomitant medication, and anticipated breakthrough medication use. The endpoint of titration is achievement of adequate pain relief, balanced against tolerability of opioid side effects. If a patient develops intolerable opioid related side effects, the methadone dose, or dosing interval, may need to be adjusted.

Dosage Adjustment During Pregnancy

Methadone clearance may be increased during pregnancy. Several small studies have demonstrated significantly lower trough methadone plasma concentrations and shorter methadone half-lives in women during their pregnancy compared to after their delivery. During pregnancy a woman’s methadone dose may need to be increased, or their dosing interval decreased. Methadone should be used in pregnancy only if the potential benefit justifies the potential risk to the fetus.

Detoxification and Maintenance Treatment of Opiate Dependence
For detoxification and maintenance of opiate dependence methadone should be administered in accordance with the treatment standards cited in 42 CFR Section 8.12, including limitations on unsupervised administration
Induction/Initial Dosing

The initial methadone dose should be administered, under supervision, when there are no signs of sedation or intoxication, and the patient shows symptoms of withdrawal. Initially, a single dose of 20 to 30 mg of methadone will often be sufficient to suppress withdrawal symptoms. The initial dose should not exceed 30 mg. If same-day dosing adjustments are to be made, the patient should be asked to wait 2 to 4 hours for further evaluation, when peak levels have been reached. An additional 5 to 10 mg of methadone may be provided if withdrawal symptoms have not been suppressed or if symptoms reappear. The total daily dose of methadone on the first day of treatment should not ordinarily exceed 40 mg. Dose adjustments should be made over the first week of treatment based on control of withdrawal symptoms at the time of expected peak activity (e.g., 2 to 4 hours after dosing). Dose adjustment should be cautious; deaths have occurred in early treatment due to the cumulative effects of the first several days’ dosing. Patients should be reminded that the dose will “hold” for a longer period of time as tissue stores of methadone accumulate.

Initial doses should be lower for patients whose tolerance is expected to be low at treatment entry. Loss of tolerance should be considered in any patient who has not taken opioids for more than 5 days. Initial doses should not be determined by previous treatment episodes or dollars spent per day on illicit drug use.

For Short-term Detoxification

For patients preferring a brief course of stabilization followed by a period of medically supervised withdrawal, it is generally recommended that the patient be titrated to a total daily dose of about 40 mg in divided doses to achieve an adequate stabilizing level. Stabilization can be continued for 2 to 3 days, after which the dose of methadone should be gradually decreased. The rate at which methadone is decreased should be determined separately for each patient. The dose of methadone can be decreased on a daily basis or at 2-day intervals, but the amount of intake should remain sufficient to keep withdrawal symptoms at a tolerable level. In hospitalized patients, a daily reduction of 20% of the total daily dose may be tolerated. In ambulatory patients, a somewhat slower schedule may be needed.

For Maintenance Treatment

Patients in maintenance treatment should be titrated to a dose at which opioid symptoms are prevented for 24 hours, drug hunger or craving is reduced, the euphoric effects of self-administered opioids are blocked or attenuated, and the patient is tolerant to the sedative effects of methadone. Most commonly, clinical stability is achieved at doses between 80 to 120 mg/day.

For Medically Supervised Withdrawal After a Period of Maintenance Treatment

There is considerable variability in the appropriate rate of methadone taper in patients choosing medically supervised withdrawal from methadone treatment. It is generally suggested that dose reductions should be less than 10% of the established tolerance or maintenance dose, and that 10 to 14-day intervals should elapse between dose reductions. Patients should be apprised of the high risk of relapse to illicit drug use associated with discontinuation of methadone maintenance treatment.

HOW SUPPLIED

Methadone Hydrochloride Tablets, USP

5 mg, round, white, scored tablets (Identified 54 210)

NDC 0054-4570-25: Bottles of 100 tablets.

NDC 0054-8553-24: Unit dose, 25 tablets per card, (reverse numbered), 4 cards per shipper.

10 mg, round, white, scored tablets (Identified 54 142)

NDC 0054-4571-25: Bottles of 100 tablets.

NDC 0054-8554-24: Unit dose, 25 tablets per card (reverse numbered), 4 cards per shipper.

Dispense in a tight, light-resistant container as defined in the USP/NF.

Store at 25°C (77°F); excursions permitted to 15°-30°C (59°-86°F) [see USP Controlled Room Temperature].

DEA order form required.

4077442//05

Revised May 2011

© RLI, 2011

Roxane Laboratories, Inc.

Columbus, Ohio 43216

PATIENT INFORMATION

METHADONE HYDROCHLORIDE TABLETS USP

5 mg, 10 mg

WARNINGS:

Keep methadone hydrochloride tablets out of the reach of children. Accidental overdose by a child is a medical emergency and can result in death. If a child accidentally takes methadone hydrochloride tablets, get emergency help right away.

Do not take a higher dose of methadone hydrochloride tablets or take it more often than prescribed. This can lead to an overdose and possible death.

Read the Patient Information that comes with methadone hydrochloride tablets before you take it and each time you get a new prescription. There may be new information. This leaflet does not take the place of talking with your doctor about your medical condition or your treatment. Share the important information in this leaflet with members of your household.

What is the Most Important Information I Should Know About Methadone Hydrochloride Tablets?

- Methadone hydrochloride tablets can cause life-threatening breathing problems which can lead to death. These problems are more likely to happen when methadone hydrochloride tablets are first started or in someone who is not already taking other narcotic (opioid) pain medicines.
- Breathing problems from methadone hydrochloride tablets may not happen right away after taking a dose. Sometimes breathing problems will happen a while after you take a dose, even after pain has returned. It is very important that you take methadone hydrochloride tablets exactly as your doctor has prescribed. Talk to your doctor about your pain. Your doctor can decide if your methadone hydrochloride tablets dose needs to be changed.
- Methadone hydrochloride tablets can cause life-threatening heartbeat problems that can lead to death. Most heartbeat problems have happened in people using large doses of methadone hydrochloride tablets for pain treatment. Some heartbeat problems have happened in people using smaller doses of methadone hydrochloride tablets for treatment of narcotic drug addiction.

What are Methadone Hydrochloride Tablets?

Methadone hydrochloride tablets are a prescription medicine that contains methadone, which is a narcotic pain medicine similar to morphine. Methadone hydrochloride tablets are a federally controlled substance (CII) because it is a strong opioid pain medicine that can be abused by people who abuse prescription medicines or street drugs.

- Prevent theft and misuse. Keep your methadone hydrochloride tablets in a safe place to protect them from theft. Never give methadone hydrochloride tablets to anyone else even if they have the same symptoms you have. It may harm them and even cause death. Selling or giving away this medicine is dangerous and against the law.

Methadone hydrochloride tablets are used:

1. to treat moderate to severe pain in people that do not respond to non-narcotic pain medicines;
2. to control withdrawal symptoms in patients being treated for narcotic drug addiction;
3. for maintenance treatment of narcotic drug addiction along with other social and medical services. Stopping maintenance treatment of narcotic drug addiction with methadone hydrochloride tablets may result in a return to narcotic drug use.

Who Should Not Take Methadone Hydrochloride Tablets?

Do not take methadone hydrochloride tablets if you:

- have severe asthma or severe lung problems.
- have a blockage or obstruction in your intestines.
- are allergic to methadone or anything else in methadone hydrochloride tablets. See the end of this leaflet for a complete list of ingredients.

What Should I Tell my Doctor Before I Start Taking Methadone Hydrochloride Tablets?

Methadone hydrochloride tablets may not be right for you. Before starting methadone hydrochloride tablets, tell your doctor about all your medical and mental conditions including a history of drug or alcohol abuse or addiction.

Tell your doctor if you:

- are pregnant or plan to become pregnant. Methadone hydrochloride tablets may harm your unborn baby.
- are breast-feeding. Methadone hydrochloride tablets pass through your breast milk and may harm your baby. You should choose to use methadone hydrochloride tablets or breast-feed, but not both.

Tell your doctor about all the medicines you take, including prescription and non-prescription medicines, vitamins, and herbal supplements. Some medicines may cause serious or life-threatening medical problems when taken with methadone hydrochloride tablets. Be especially careful about other medicines that may make you sleepy, such as other pain medicines, anti-depressant medicines, sleeping pills, anxiety medicines, antihistamines, or tranquilizers. Sometimes, the doses of certain medicines (including methadone hydrochloride tablets) may need to be changed if they are used together.

Do not take any medicine while using methadone hydrochloride tablets until you have first talked to your doctor or pharmacist. They will be able to tell you if it is safe to take other medicines while you are using methadone hydrochloride tablets.

Know the medicines you take. Keep a list of your medicines and show it to your doctor and pharmacist each time you get a new medicine.

How Should I Take Methadone Hydrochloride Tablets?

- Take methadone hydrochloride tablets exactly as prescribed. Follow your doctor's directions exactly. Your doctor may change your dose based on your reactions to the medicine. Do not change your dose unless your doctor tells you to change it. Do not take a higher dose of methadone hydrochloride tablets or take it more often than prescribed. This can lead to an overdose and possibly death.
- If you take too much methadone hydrochloride tablets or overdose, call 911 or your local emergency number right away.
- Review your medical conditions regularly with your doctor to determine if you still need methadone hydrochloride tablets, or if the dose needs to be adjusted.
- When starting treatment with methadone hydrochloride tablets for narcotic drug dependence, you should be aware that your dose of methadone will “hold” for longer periods of time as treatment goes on.
- Stopping methadone hydrochloride tablets. Ask your doctor for instructions on how to stop this medicine slowly to avoid uncomfortable symptoms. You should not stop taking methadone hydrochloride tablets all at once if you have been taking it for more than a few days.
- Tell all health professionals that treat you that you take methadone hydrochloride tablets.
- After stopping treatment with methadone hydrochloride tablets, flush the unused tablets down the toilet.

What Should I Avoid While Taking Methadone Hydrochloride Tablets?

- Do not drive, operate heavy machinery, or do other possible dangerous activities until you know how methadone hydrochloride tablets affect you. Methadone hydrochloride tablets can make you sleepy. Ask your doctor when it is okay to do these activities.
- Do not drink alcohol while using methadone hydrochloride tablets. It may increase the chance of having dangerous side effects.
- Do not take other medicines with methadone hydrochloride tablets without first talking with your doctor.

What are the Possible Side Effects of Methadone Hydrochloride Tablets?

- Methadone hydrochloride tablets can cause life-threatening breathing and heart problems which can lead to death. See “What is the Most Important Information I Should Know About Methadone Hydrochloride Tablets?”
  - Call your doctor or get medical help right away if you:
    - have trouble breathing.
    - have extreme drowsiness and breathing slows down.
    - have slow shallow breathing (little chest movement with breathing).
    - fast or slowed heartbeat.
    - feel faint, very dizzy, confused, have palpitations (irregular heartbeat) or any other unusual symptoms.

These can be symptoms that you have taken too much (overdose of) methadone hydrochloride tablets, or the dose is too high for you. They can also be symptoms of a serious heart reaction. These symptoms can lead to serious problems or death if not treated right away.

- Methadone hydrochloride tablets can cause your blood pressure to drop. This can make you feel dizzy if you get up too fast from sitting or lying down.
- Methadone hydrochloride tablets can cause physical dependence. Do not stop taking methadone hydrochloride tablets or any other opioid without first talking to your doctor. You could become sick with uncomfortable withdrawal symptoms because your body has become used to these medicines. Talk to your doctor about slowly stopping methadone hydrochloride tablets to avoid getting sick with withdrawal symptoms. Physical dependency is not the same as drug addiction.
- For patients using methadone hydrochloride tablets for pain treatment, there is a chance of abuse or addiction with methadone hydrochloride tablets. The chance is higher if you are or have been addicted to or abused other medicines, street drugs, or alcohol, or if you have a history of mental problems.

Some common side effects of methadone hydrochloride tablets are lightheadedness, dizziness, drowsiness, nausea, vomiting and sweating. Other side effects include weakness, headache, constipation, itching, and dry mouth.

Talk to your doctor about any side effects that bother you or that do not go away.

These are not all the possible side effects of methadone hydrochloride tablets. For a complete list, ask your doctor or pharmacist.

How Should I Store Methadone Hydrochloride Tablets?

- Keep methadone hydrochloride tablets in a safe place away from children. Accidental use by a child is a medical emergency that can result in death. If a child accidentally takes methadone hydrochloride tablets, get emergency help right away.
- Keep methadone hydrochloride tablets at room temperature, 68° to 77°F (20° to 25°C).
- Always keep methadone hydrochloride tablets in a secure place to protect from theft.
- Dispose of any unused methadone hydrochloride tablets remaining from a prescription as soon as they are no longer needed. Unused tablets should be flushed down the toilet.

General Information About Methadone Hydrochloride Tablets

Medicines are sometimes prescribed for purposes other than those listed in patient information leaflet. Do not use methadone hydrochloride tablets for a condition for which it was not prescribed. Do not give methadone hydrochloride tablets to other people, even if they have the same symptoms you have. Methadone hydrochloride tablets can harm other people and even cause death. Sharing methadone hydrochloride tablets is against the law.

This leaflet summarizes the most important information about methadone hydrochloride tablets. If you would like more information, talk with your doctor. You can ask your doctor or pharmacist for information about methadone hydrochloride tablets that was written for healthcare professionals, or you can visit www.Mallinckrodt.com or call 1-800-778-7898.

What are the Ingredients in Methadone Hydrochloride Tablets?

Call your doctor for medical advice about side effects. You may report side effects to FDA at 1-800-FDA-1088.

Active Ingredient: methadone hydrochloride, USP

Inactive Ingredients: magnesium stearate, microcrystalline cellulose, and starch.

4077442//05

Revised May 2011

© RLI, 2011